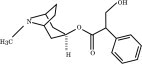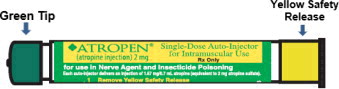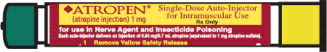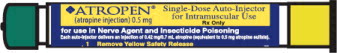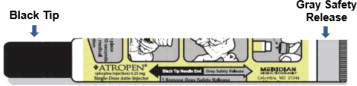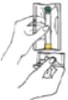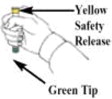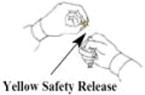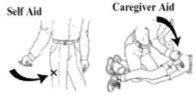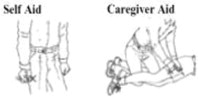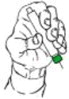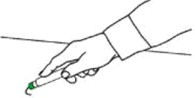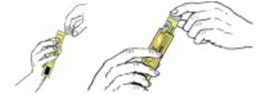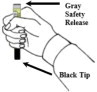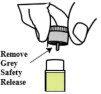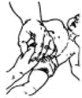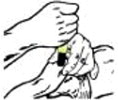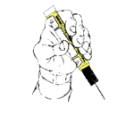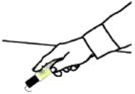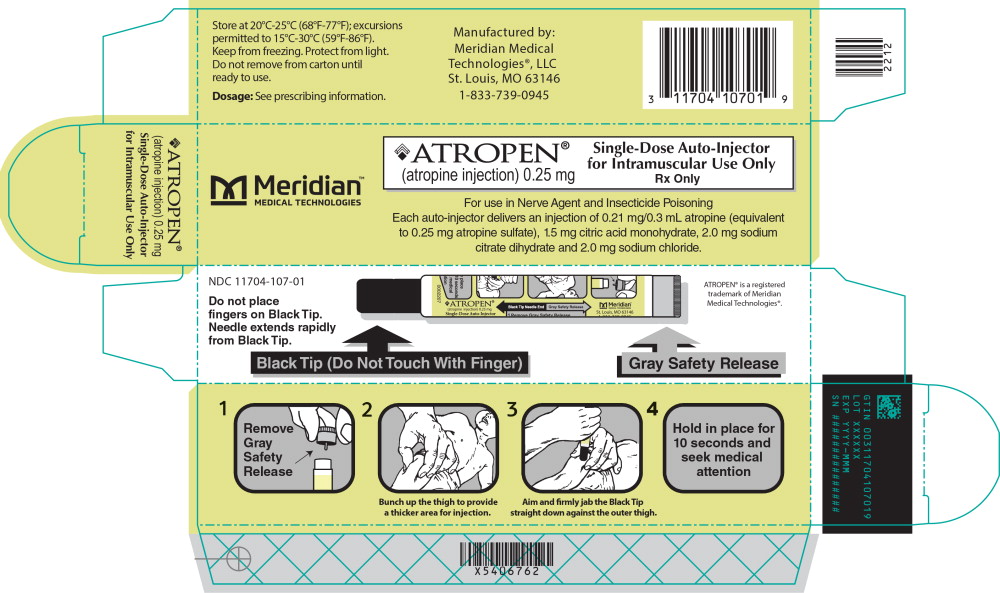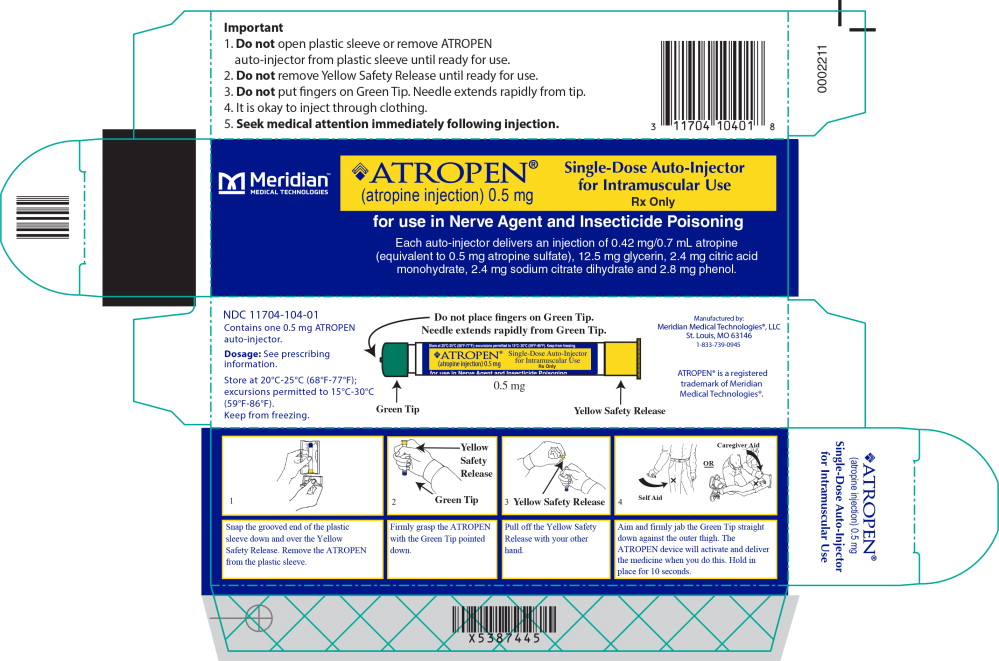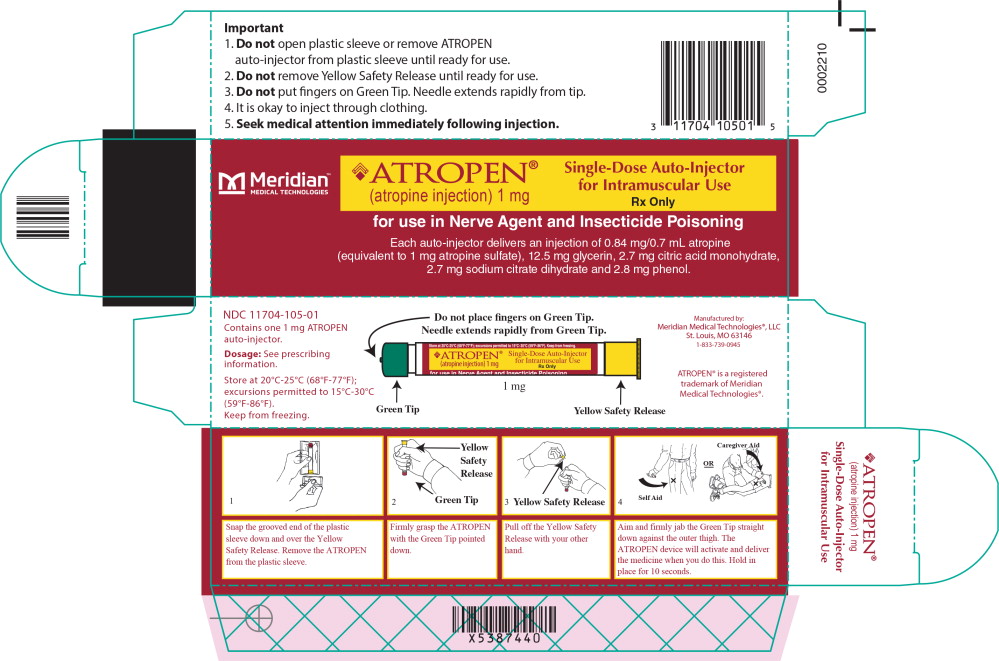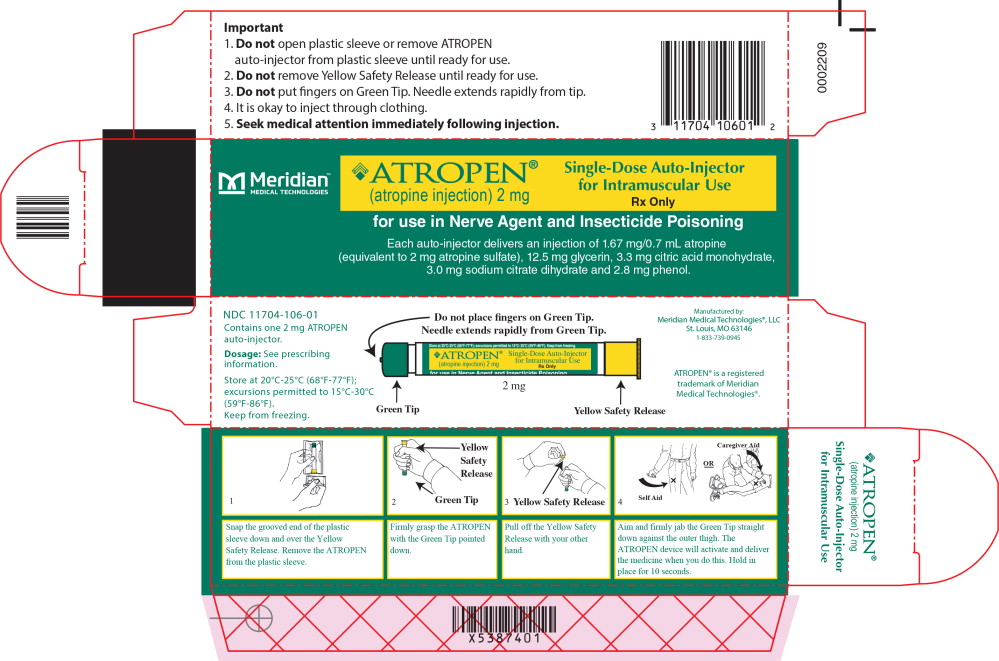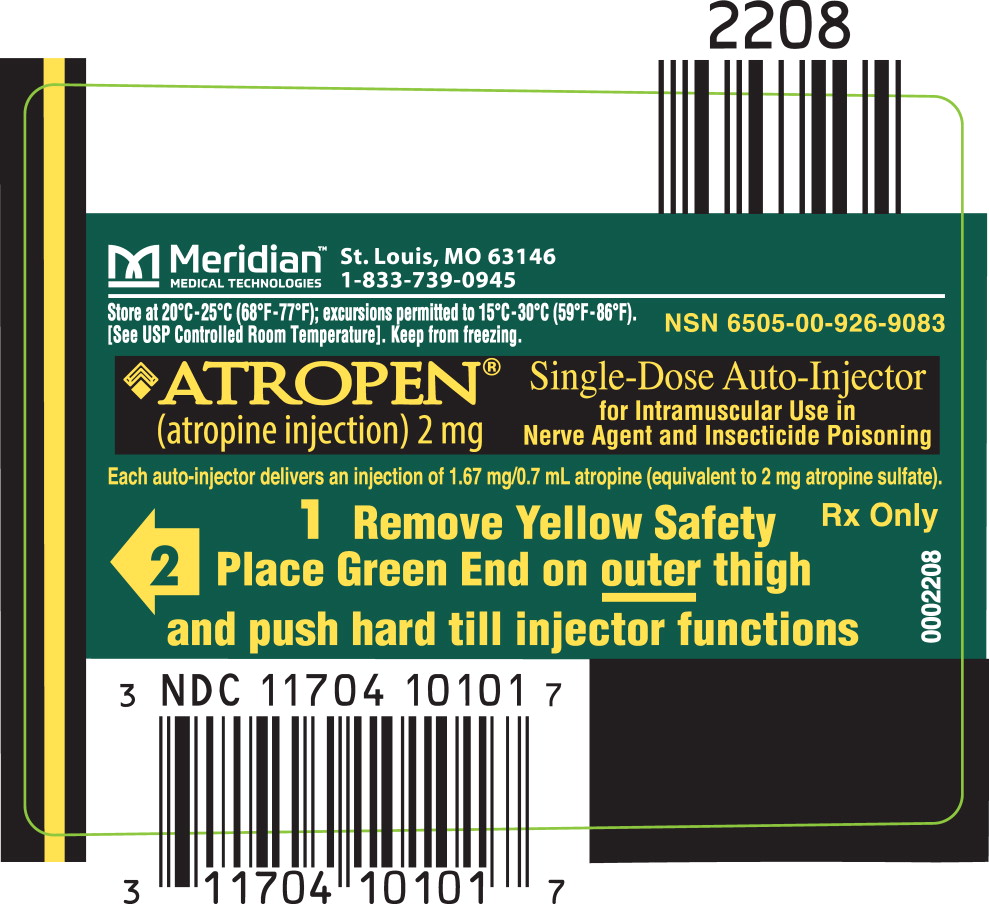 DRUG LABEL: ATROPEN Auto-Injector
NDC: 11704-107 | Form: INJECTION
Manufacturer: Meridian Medical Technologies LLC
Category: prescription | Type: HUMAN PRESCRIPTION DRUG LABEL
Date: 20220915

ACTIVE INGREDIENTS: atropine 0.25 mg/0.3 mL
INACTIVE INGREDIENTS: citric acid monohydrate; water; sodium citrate, unspecified form; Nitrogen; sodium chloride

HIGHLIGHTS OF PRESCRIBING INFORMATION

These highlights do not include all the information needed to use ATROPEN® safely and effectively. See full prescribing information for ATROPEN.
ATROPEN (atropine injection), for intramuscular use
Initial U.S. Approval: 1960

1 INDICATIONS AND USAGE

ATROPEN is a cholinergic muscarinic antagonist indicated for the treatment of poisoning by susceptible organophosphorus nerve agents having cholinesterase activity as well as organophosphorus or carbamate insecticides in adult and pediatric patients. (1)

2 DOSAGE AND ADMINISTRATION

- ATROPEN is a single-dose autoinjector intended as an initial treatment of the muscarinic symptoms of insecticide or nerve agent poisonings; definitive medical care should be sought immediately. (2.1)
- Dosage is dependent on weight. (2.2)
- Dosage for Mild Symptoms: If the patient experiences two or more mild symptoms, administer one injection intramuscularly into the mid-lateral thigh. If, at any time after the first dose, the patient develops any of the severe symptoms, administer two additional injections intramuscularly in rapid succession. (2.2)
- Dosage for Severe Symptoms: If the patient is either unconscious or has any of the severe symptoms, immediately administer three injections intramuscularly into the patient's mid-lateral thigh in rapid succession. (2.2)

3 DOSAGE FORMS AND STRENGTHS

Injection: Each prefilled single-dose autoinjector contains atropine in a self-contained unit, and is available in four strengths 0.25 mg/0.3 mL, 0.5 mg/0.7 mL, 1 mg/0.7 mL, and 2 mg/0.7 mL. (3)

4 CONTRAINDICATIONS

None.

5 WARNINGS AND PRECAUTIONS

- Cardiovascular (CV) Risks: Tachycardia, palpitations, premature ventricular contractions, flutter, fibrillation, etc. Use caution in patients with known CV disease or conduction problems. (5.1)
- Heat Injury: May inhibit sweating and lead to hyperthermia; avoid excessive exercising and heat exposure. (5.2)
- Acute Glaucoma: May precipitate in susceptible individuals. (5.3)
- Urinary Retention: May precipitate in patient with bladder outflow obstruction. (5.4)
- Pyloric Stenosis: May precipitate complete obstruction. (5.5)
- Exacerbation of Chronic Lung Disease: Atropine may cause inspissation of bronchial secretions and formation of dangerous viscid plugs in individuals with chronic lung disease; monitor respiratory status. (5.6)
- Hypersensitivity: Atropine may cause hypersensitivity reactions, including anaphylaxis. (5.7)

6 ADVERSE REACTIONS

Mild to moderate pain may be experienced at the site of injection. Common adverse reactions of atropine include dryness of mouth, blurred vision, dry eyes, photophobia, confusion, headache, dizziness, tachycardia, palpitations, flushing, urinary hesitance or retention, constipation, abdominal pain, abdominal distention, nausea, vomiting, loss of libido, and impotency. (6)

To report SUSPECTED ADVERSE REACTIONS, contact Meridian Medical Technologies®, LLC at 1-833-739-0945 or FDA at 1-800-FDA-1088 or www.fda.gov/medwatch.

7 DRUG INTERACTIONS

- Pralidoxime: The signs of atropinization (flushing, mydriasis, tachycardia, dryness of the mouth and nose) may occur earlier than might be expected than when atropine is used alone. (7.1)
- Barbiturates: Atropine may potentiate the effect of barbiturates. (7.2)

8 USE IN SPECIFIC POPULATIONS

Geriatric patients may be more susceptible to the effects of atropine. (8.5)

FULL PRESCRIBING INFORMATION

1 INDICATIONS AND USAGE

ATROPEN is indicated for the treatment of poisoning by susceptible organophosphorus nerve agents having cholinesterase activity as well as organophosphorus or carbamate insecticides in adult and pediatric patients.

2 DOSAGE AND ADMINISTRATION

2.1 Important Administration Information

- It is recommended that three ATROPEN autoinjectors be available for use in each patient at risk for organophosphorus or carbamate poisoning; one (1) for mild symptoms plus two (2) more for severe symptoms [see Dosage and Administration (2.2)]. Different dose strengths of ATROPEN are available depending on the patient's weight.
- ATROPEN should be used by persons who have had adequate training in the recognition and treatment of nerve agent or insecticide intoxication, but may be administered by a caregiver or self-administration if a trained provider is not available.
- Only administer ATROPEN to patients experiencing symptoms of organophosphorus or carbamate poisoning in a situation where exposure is known or suspected. ATROPEN is a single-dose autoinjector intended as an initial treatment of the muscarinic symptoms of insecticide or nerve agent poisonings (generally breathing difficulties due to increased secretions); definitive medical care should be sought immediately.
- ATROPEN should be administered as soon as symptoms of organophosphorus or carbamate poisoning appear.
- In severe poisonings, it may also be desirable to concurrently administer an anticonvulsant (preferably a benzodiazepine) if seizure is suspected in the unconscious individual since the classic tonic-clonic jerking may not be apparent due to the effects of the poison.
- A cholinesterase reactivator such as pralidoxime may serve as an important adjunct to atropine therapy.
- Close supervision of all treated patients is indicated for at least 48 to 72 hours.
- Parenteral drug products should be inspected visually for particulate matter and discoloration prior to administration, whenever solution and container permit [see Dosage Forms and Strengths (3)].

2.2 Dosage Information

Different dose strengths of ATROPEN are available depending on the patient's age and weight (see Table 1).

Table 1: Recommended Dose Strength per ATROPEN Injection
Age and Body Weight | Strength of each ATROPEN Injection
Adults and pediatric patients weighing over 41 kg (90 pounds) (generally over 10 years of age) | ATROPEN 2 mg (green label)
Pediatric patients weighing 18 kg to 41 kg (40 pounds to 90 pounds) (generally 4 to 10 years of age) | ATROPEN 1 mg (red label)
Pediatric patients weighing 7 kg to 18 kg (15 pounds to 40 pounds) (generally 6 months to 4 years of age) | ATROPEN 0.5 mg (blue label)
Pediatric patients weighing less than 7 kg (15 pounds) (generally less than 6 months of age) | ATROPEN 0.25 mg (yellow label)

Dosage for Mild Symptoms

First Dose: If the patient experiences two or more mild symptoms of nerve agent or insecticide exposure listed in Table 2, administer one (1) ATROPEN injection intramuscularly into the mid-lateral (outer) thigh.

Additional Doses: If, at any time after receiving the first ATROPEN injection, the patient has any of the severe symptoms listed in Table 2, administer two (2) additional ATROPEN injections in rapid succession. If possible, a person other than the patient should administer the second and third ATROPEN injections.

Wait 10 to 15 minutes for ATROPEN to take effect. If after 10 to 15 minutes, the patient does not develop any of the severe symptoms listed in Table 2, no additional ATROPEN injections are recommended.

Dosage for Severe Symptoms

If the patient is either unconscious or has any of the severe symptoms listed in Table 2, immediately administer three (3) ATROPEN injections intramuscularly into the patient's mid-lateral thigh in rapid succession.

Table 2: Common Symptoms of Organophosphorus or Carbamate Poisoning
Mild Symptoms | Severe Symptoms
- Blurred vision, miosis - Excessive, unexplained teary eyes* - Excessive, unexplained runny nose* - Increased salivation such as sudden unexplained excessive drooling* - Chest tightness or difficulty breathing - Tremors throughout the body or muscular twitching - Nausea and/or vomiting - Unexplained wheezing, coughing or increased airway secretions - Acute onset of stomach cramps - Tachycardia or bradycardia | - Strange or confused behavior - Severe difficulty breathing or copious secretions from lungs/airway - Severe muscular twitching and general weakness** - Involuntary urination and defecation* - Convulsions - Unconsciousness
* These symptoms are sometimes observed in healthy infants and young children. In this age group, these symptoms are less reliable than other symptoms listed. Symptoms must be considered collectively when nerve agent or pesticide exposure is known or suspected.
** Infants may become drowsy or unconscious, with muscle floppiness rather than muscle twitching, soon after exposure to nerve agents or insecticides.

2.3 Administration Instructions

Directions for the Use of 2 mg, 1 mg, and 0.5 mg ATROPEN

1. Snap the grooved end of the plastic sleeve down and over the Yellow Safety Release. Remove the ATROPEN autoinjector from the plastic sleeve. Do not place fingers on the Green Tip.
2. Firmly grasp the ATROPEN autoinjector with the Green Tip (needle end) pointed down.
3. With your other hand, pull off the Yellow Safety Release. ATROPEN is now ready to be administered.
4. Aim and firmly jab the Green Tip straight down (at a 90° angle) against the mid-lateral thigh. The ATROPEN device will activate and deliver the medicine when you do this. ATROPEN can inject through clothing, but make sure pockets at the injection site are empty. Very thin people and small children should also be injected in the mid-lateral thigh, but before giving ATROPEN, bunch up the thigh to provide a thicker area for injection.
5. Hold the ATROPEN autoinjector firmly in place for at least 10 seconds to allow the injection to finish.
6. Remove the ATROPEN autoinjector and massage the injection site for several seconds. If the needle is not visible, check to be sure the Yellow Safety Release has been removed, and repeat steps 4 and 5, but press harder.
7. After use, using a hard surface, bend the needle back against the ATROPEN autoinjector and either pin the used ATROPEN autoinjectors to the patient's clothing or show the used ATROPEN autoinjectors to the first medical person you see. This will allow medical personnel to see the number and dose of ATROPEN autoinjectors administered. Move yourself and the patient away from the contaminated area right away. Try to find medical help.

Directions for the Use of 0.25 mg ATROPEN

1. Remove the plastic cap from the yellow tube and slide the ATROPEN autoinjector from the tube. Do not place fingers on the Black Tip.
2. Firmly grasp the ATROPEN autoinjector with the Black Tip (needle end) pointed down.
3. With your other hand, pull off the Gray Safety Release. ATROPEN is now ready to be administered.
4. Bunch up the thigh to provide a thicker area for injection. Aim and firmly jab the Black Tip straight down (at a 90° angle) against the mid-lateral thigh. The ATROPEN device will activate and deliver the medicine when you do this.
5. Hold the ATROPEN autoinjector firmly in place for at least 10 seconds to allow the injection to finish.
6. Remove the ATROPEN autoinjector and massage the injection site for several seconds. If the needle is not visible, check to be sure the Gray Safety Release has been removed, and repeat steps 4 and 5, but press harder.
7. After use, using a hard surface, bend the needle back against the ATROPEN autoinjector and either pin the used ATROPEN autoinjectors to the patient's clothing or show the used ATROPEN autoinjectors to the first medical person you see. This will allow medical personnel to see the number and dose of ATROPEN autoinjectors administered. Move yourself and the patient away from the contaminated area right away. Try to find medical help.

3 DOSAGE FORMS AND STRENGTHS

Injection: Each single-dose ATROPEN autoinjector contains a clear sterile solution of atropine. Four strengths of ATROPEN are available

- 0.25 mg/0.3 mL (yellow label): 0.21 mg atropine (equivalent to 0.25 mg atropine sulfate) in 0.3 mL
- 0.5 mg/0.7 mL (blue label): 0.42 mg atropine (equivalent to 0.5 mg atropine sulfate) in 0.7 mL
- 1 mg/0.7 mL (red label): 0.84 mg atropine (equivalent to 1 mg atropine sulfate) in 0.7 mL
- 2 mg/0.7 mL (green label): 1.67 mg atropine (equivalent to 2 mg atropine sulfate) in 0.7 mL

4 CONTRAINDICATIONS

None.

5 WARNINGS AND PRECAUTIONS

5.1 Cardiovascular Risks

Cardiovascular adverse reactions reported in the literature for atropine include, but are not limited to, sinus tachycardia, palpitations, premature ventricular contractions, atrial flutter, atrial fibrillation, ventricular flutter, ventricular fibrillation, cardiac syncope, asystole, and myocardial infarction [see Adverse Reactions (6)]. In patients with a recent myocardial infarction and/or severe coronary artery disease, there is a possibility that atropine-induced tachycardia may cause ischemia, extend or initiate myocardial infarcts, and stimulate ventricular ectopy and fibrillation. ATROPEN should be used with caution in patients with known cardiovascular disease or cardiac conduction problems.

5.2 Heat Injury

ATROPEN may inhibit sweating which, in a warm environment or with excessive exercise, can lead to hyperthermia and heat injury. To the extent feasible, avoid excessive exercise and heat exposure [see Adverse Reactions (6), Overdosage (10)].

5.3 Acute Glaucoma

ATROPEN may cause acute glaucoma and should be administered with caution in patients at risk for acute glaucoma or who have severe narrow angle glaucoma. Monitor for signs and symptoms of intraocular pressure, as appropriate.

5.4 Urinary Retention

ATROPEN may cause urinary retention and should be administered with caution to patients with clinically significant bladder outflow obstruction.

5.5 Pyloric Stenosis

ATROPEN may cause complete pyloric obstruction in patients with partial pyloric stenosis. These patients should be monitored for gastrointestinal symptoms following administration of ATROPEN.

5.6 Exacerbation of Chronic Lung Disease

Atropine may cause thickening of bronchial secretions and formation of dangerous viscid plugs in individuals with chronic lung disease. Respiratory status should be monitored in individuals with chronic lung disease following administration of ATROPEN.

5.7 Hypersensitivity

Atropine can cause hypersensitivity reactions, including anaphylactic reactions [see Adverse Reactions (6)]. Medical supervision is necessary in patients who have had previous anaphylactic reactions to atropine and require treatment for organophosphorus or nerve agent poisoning.

6 ADVERSE REACTIONS

The following serious adverse reactions are described elsewhere in the labeling:

- Cardiovascular Risks [see Warnings and Precautions (5.1)]
- Heat Injury [see Warnings and Precautions (5.2)]
- Acute Glaucoma [see Warnings and Precautions (5.3)]
- Urinary Retention [see Warnings and Precautions (5.4)]
- Pyloric Stenosis [see Warnings and Precautions (5.5)]
- Exacerbation of Chronic Lung Disease [see Warnings and Precautions (5.6)]
- Hypersensitivity [see Warnings and Precautions (5.7)]

The following adverse reactions associated with the use of atropine were identified in the literature. Because these reactions are reported voluntarily from a population of uncertain size, it is not always possible to reliably estimate their frequency or establish a causal relationship to drug exposure.

Adverse Reactions at Recommended Doses

Common adverse reactions of atropine can be attributed to its antimuscarinic action. These include dryness of the mouth, blurred vision, dry eyes, photophobia, confusion, headache, dizziness, tachycardia, palpitations, flushing, urinary hesitancy or retention, constipation, abdominal pain, abdominal distention, nausea and vomiting, loss of libido, and impotence. Anhidrosis may produce heat intolerance and impairment of temperature regulation in a hot environment. Dysphagia, paralytic ileus, acute angle closure glaucoma, maculopapular rash, petechial rash, and scarlatiniform rash have also been reported. Adverse cardiac reactions, including arrhythmias and myocardial infarction, have been reported with atropine [see Warnings and Precautions (5.1), Clinical Pharmacology (12.2)].

Larger doses of atropine may produce central nervous system effects such as restlessness, tremor, fatigue, locomotor difficulties, delirium, hallucinations, depression and ultimately, medullary paralysis and death [see Overdosage (10)]. Large doses can also lead to circulatory collapse. In such cases, blood pressure declines and death due to respiratory failure may ensue following paralysis and coma.

Hypersensitivity

Hypersensitivity reactions will occasionally occur with atropine; these are usually seen as skin rashes and may progress to exfoliation. Anaphylactic reaction and laryngospasm have also occurred.

Pediatric Patients

Adverse events seen in pediatrics are similar to those that occur in adult patients although central nervous system complaints are often seen earlier and at lower doses.

Additional Adverse Reactions to Atropine by Organ System

The following adverse reactions were reported in published literature for atropine in both adults and children:

Cardiovascular: Sinus tachycardia, supraventricular tachycardia, junctional tachycardia, ventricular tachycardia, bradycardia, palpitations, ventricular arrhythmia, ventricular flutter, ventricular fibrillation, atrial arrhythmia, atrial fibrillation, atrial ectopic beats, ventricular premature contractions, bigeminal beats, trigeminal beats, nodal extrasystole, ventricular extrasystole, supraventricular extrasystole, asystole, cardiac syncope, prolongation of sinus node recovery time, cardiac dilation, left ventricular failure, myocardial infarction, intermittent nodal rhythm (no P wave), prolonged P wave, shortened PR segment, R on T phenomenon, shortened RT duration, widening and flattening of QRS complex, prolonged QT interval, flattening of T wave, repolarization abnormalities, altered ST-T waves, retrograde conduction, transient atrioventricular (AV) dissociation, increased blood pressure, decreased blood pressure, labile blood pressure, weak or impalpable peripheral pulses.

Eye: Mydriasis, blurred vision, pupils poorly reactive to light, photophobia, decreased contrast sensitivity, decreased visual acuity, decreased accommodation, cycloplegia, strabismus, heterophoria, cyclophoria, acute angle closure glaucoma, conjunctivitis, keratoconjunctivitis sicca, blindness, tearing, dry eyes/dry conjunctiva, irritated eyes, crusting of eyelid, blepharitis.

Gastrointestinal: Nausea, abdominal pain, paralytic ileus, decreased bowel sounds, distended abdomen, vomiting, delayed gastric emptying, decreased food absorption, dysphagia.

General: Hyperpyrexia, lethargy, somnolence, chest pain, excessive thirst, weakness, syncope, insomnia, tongue chewing, dehydration, feeling hot, injection site reaction.

Immunologic: Anaphylactic reaction.

Special Investigations: Leukocytosis, hyponatremia, elevated blood urea nitrogen (BUN), elevated hemoglobin, elevated erythrocytes, low hemoglobin, hypoglycemia, hyperglycemia, hypokalemia, increase in photic stimulation on electroencephalogram (EEG), signs of drowsiness on EEG, runs of alpha waves on EEG, alpha waves (EEG) blocked upon opening eyes.

Metabolic: Failure to feed.

Central Nervous System: Ataxia, hallucinations (visual or aural), seizures (generally tonic-clonic), abnormal movements, coma, confusion, stupor, dizziness, amnesia, headache, diminished tendon reflexes, hyperreflexia, muscle twitching, opisthotonos, Babinski's reflex/Chaddock's reflex, hypertonia, dysmetria, muscle clonus, sensation of intoxication, difficulty concentrating, vertigo, dysarthria.

Psychiatric: Agitation, restlessness, delirium, paranoia, anxiety, mental disorders, mania, withdrawn behavior, behavior changes.

Genitourinary: Difficulty in micturition, urine urgency, distended urinary bladder, urine retention, bed-wetting.

Pulmonary: Tachypnea, slow respirations, shallow respirations, breathing difficulty, labored respirations, inspiratory stridor, laryngitis, laryngospasm, pulmonary edema, respiratory failure, subcostal recession.

Dermatologic: Dry mucous membranes, dry warm skin, flushed skin, oral lesions, dermatitis, petechiae, rash, macular rash, papular rash, maculopapular rash, scarlatiniform rash, erythematous rash, sweating/moist skin, cold skin, cyanosed skin, salivation.

Injection Site

Muscle tightness and pain may occur at the injection site.

Inadvertent Injection

In cases where ATROPEN is inadvertently administered to people who are not poisoned with nerve agent or organophosphorus insecticide, the following effects on their ability to function normally may occur. Patients with cardiac disease may be at risk for serious adverse events, including death.

Atropine 2 mg IM, when given to healthy male volunteers, is associated with minimal effects on visual, motor, and mental functions, though unsteadiness walking and difficulty concentrating may occur. Atropine reduces body sweating and increases body temperature, particularly with exercise and under hot conditions.

Atropine 4 mg IM, when given to healthy male volunteers, is associated with impaired visual acuity, visual near point accommodation, logical reasoning, digital recall, learning, and cognitive reaction time. Ability to read is reduced or lost. Subjects are unsteady and need to concentrate on walking. These effects begin about 15 minutes to one hour or more post-dose.

Atropine 6 mg IM, when given to healthy male volunteers, is associated with the effects described above plus additional central nervous system effects including poor coordination, poor attention span, and visual hallucinations (colored flashes) in many subjects. Frank visual hallucinations, auditory hallucinations, disorientation, and ataxia occur in some subjects. Skilled and labor-intense tasks are performed more slowly and less efficiently. Decision making takes longer and is sometimes impaired.

It is unclear if the above data, obtained from studies of healthy adult subjects, can be extrapolated to other populations. In the elderly and patients with co-morbid conditions, the effects of ≥2 mg atropine on the ability to see, walk, and think properly are unstudied; effects may be greater in susceptible populations.

Patients who are mistakenly injected with ATROPEN should avoid potentially dangerous overheating, avoid vigorous physical activity, and seek medical attention as soon as feasible.

Adverse Reactions Observed in Pediatric Patients after Inappropriate Administration of ATROPEN

Amitai et el (JAMA 1990) evaluated the safety of ATROPEN 0.5 mg, 1 mg, and 2 mg in a case series of 240 children who received ATROPEN inappropriately (i.e., no nerve agent exposure) during the 1990 Gulf War Period. Overall, severity of atropinization followed a nonlinear correlation with dose. Estimated doses up to 0.045 mg/kg produced no signs of atropinization. Estimated doses between 0.045 mg/kg to 0.175 mg/kg and even greater than 0.175 mg/kg were associated with mild and severe effects, respectively. Actual dosage received by children may have been considerably lower than estimated since incomplete injection in many cases was suspected. Regardless, adverse events reported were generally mild and self-limited. Few children required hospitalization. Adverse reactions reported were dilated pupils (43%), tachycardia (39%), dry membranes (35%), flushed skin (20%), temperature 37.8°C or 100°F (4%), and neurologic abnormalities (5%). There was also local pain and swelling. In 91 children with electrocardiograms (ECGs), no abnormalities were noted other than sinus tachycardia; 22 children had severe tachycardia of 160 bpm to 190 bpm. Neurologic abnormalities consisted of irritability, agitation, confusion, lethargy, and ataxia

7 DRUG INTERACTIONS

7.1 Pralidoxime

When atropine and pralidoxime are used together, the signs of atropinization (flushing, mydriasis, tachycardia, dryness of the mouth and nose) may occur earlier than might be expected when atropine is used alone because pralidoxime may potentiate the effect of atropine. Excitement and manic behavior immediately following recovery of consciousness have been reported in several cases. However, similar behavior has occurred in cases of organophosphate poisoning that were not treated with pralidoxime.

7.2 Barbiturates

Barbiturates are potentiated by the anticholinesterases; therefore, barbiturates should be used cautiously in the treatment of convulsions resulting from exposure to atropine.

8 USE IN SPECIFIC POPULATIONS

8.1 Pregnancy

Risk Summary

Atropine readily crosses the placental barrier and enters fetal circulation. There are no adequate data on the developmental risk associated with the use of atropine in pregnant women. Adequate animal reproduction studies have not been conducted with atropine. In the U.S. general population, the estimated background risk of major birth defects and miscarriage in clinically recognized pregnancies is 2% to 4% and 15% to 20%, respectively.

8.2 Lactation

Risk Summary

Atropine has been reported to be excreted in human milk. There are no data on the effects of atropine on the breastfed infant or the effects of the drug on milk production. The developmental and health benefits of breastfeeding should be considered along with the mother's clinical need for ATROPEN and any potential adverse effects on the breastfed infant from ATROPEN or from the underlying maternal condition.

8.4 Pediatric Use

A review of published literature supports the safety and effectiveness of atropine in the setting of organophosphate insecticide poisoning in all pediatric age groups.

Adverse events seen in pediatric patients treated with atropine are similar to those that occur in adult patients, although central nervous system effects are often seen earlier and at lower doses [see Adverse Reactions (6)].

Overheating (atropine fever) caused by suppression of sweat gland activity may be more pronounced in infants and small children. Extreme hyperthermia in a newborn has been reported with as little as 0.065 mg orally.

8.5 Geriatric Use

Geriatric patients may be more susceptible to the effects of atropine. Because of the longer half-life of atropine in geriatric patients, they may require less frequent doses after the initial dose [see Clinical Pharmacology (12.3)].

10 OVERDOSAGE

Symptoms

Manifestations of atropine overdose are dose-related and include flushing, dry skin and mucous membranes, tachycardia, widely dilated pupils that are poorly responsive to light, blurred vision, and fever (which can sometimes be dangerously elevated). Locomotor difficulties, disorientation, hallucinations, delirium, confusion, agitation, coma, and central depression can occur and may last 48 hours or longer. In instances of severe atropine intoxication, respiratory depression, coma, circulatory collapse, and death may occur.

Treatment

For atropine overdose, supportive treatment should be administered. If respiration is depressed, artificial respiration with oxygen is necessary. Ice bags, a hypothermia blanket, or other methods of cooling may be required to reduce atropine-induced fever, especially in pediatric patients [see Use in Specific Populations (8.4)]. Catheterization may be necessary if urinary retention occurs. Since atropine elimination takes place through the kidney, urinary output must be maintained and increased if possible: intravenous fluids may be indicated. Because of atropine-induced photophobia, the room should be darkened.

A benzodiazepine may be needed to control marked excitement and convulsions. However, large doses for sedation should be avoided because the central nervous system depressant effect may coincide with the depressant effect occurring late in severe atropine poisoning. Barbiturates are potentiated by the anticholinesterases; therefore, barbiturates should be used cautiously in the treatment of convulsions. Central nervous system stimulants are not recommended.

11 DESCRIPTION

Each prefilled ATROPEN single-dose autoinjector provides an intramuscular dose of atropine, a cholinergic muscarinic antagonist in a self-contained unit, designed for self- or caregiver-administration.

When activated, the ATROPEN 0.25 mg autoinjector delivers 0.21 mg atropine base (equivalent to 0.25 mg atropine sulfate) in 0.3 mL of sterile pyrogen-free solution containing citrate buffer, sodium chloride, and Water for Injection. The pH range is 4.0 to 5.0.

When activated, the ATROPEN 0.5 mg autoinjector delivers 0.42 mg atropine base (equivalent to 0.5 mg atropine sulfate), the ATROPEN 1 mg autoinjector delivers 0.84 mg atropine base (equivalent to 1 mg atropine sulfate), and the ATROPEN 2 mg autoinjector delivers 1.67 mg atropine base (equivalent to 2 mg atropine sulfate). Each 0.5 mg, 1 mg, and 2 mg ATROPEN autoinjector delivers atropine in 0.7 mL of sterile pyrogen-free solution containing 12.5 mg glycerin, 2.8 mg phenol, citrate buffer, and Water for Injection. The pH range is 4.0 to 5.0.

Atropine occurs as white crystals, usually needle-like, or as a white, crystalline powder. It is slightly soluble in water with a molecular weight of 289.38. Atropine, a naturally occurring belladonna alkaloid, is a racemic mixture of equal parts of d- and l-hyoscyamine, with activity due almost entirely to the levo isomer of the drug.

Chemically, atropine is designated as 1αH,5αH-Tropan-3α-ol (±) tropate (ester). Its empirical formula is C17H23NO3 and its structural formula is as follows:

12 CLINICAL PHARMACOLOGY

12.1 Mechanism of Action

Atropine competitively blocks the effects of acetylcholine, including excess acetylcholine due to organophosphorus poisoning, at muscarinic cholinergic receptors on smooth muscle, cardiac muscle, secretory gland cells, and in peripheral autonomic ganglia and the central nervous system.

12.2 Pharmacodynamics

Atropine reduces secretions in the mouth and respiratory passages, relieves airway constriction, and may reduce centrally-mediated respiratory paralysis. In severe organophosphorus poisoning, a fully atropinized patient may develop or continue to have respiratory failure and may require artificial respiration and suctioning of airway secretions. Atropine may cause thickening of secretions.

Atropine-induced parasympathetic inhibition may be preceded by a transient phase of stimulation, especially on the heart where small doses first slow the rate before characteristic tachycardia develops due to paralysis of vagal control. Atropine increases heart rate and reduces atrioventricular conduction time. Adequate atropine doses can prevent or abolish bradycardia or asystole produced by organophosphorus nerve agents.

Atropine may decrease the degree of partial heart block, which can occur after organophosphorus poisoning. In some patients with complete heart block, atropine may accelerate the idioventricular rate; in others, the rate is stabilized. In some patients with conduction defects, atropine may cause paradoxical atrioventricular block and nodal rhythm.

Atropine will not act on the neuromuscular junction and has no effect on muscle paralysis or weakness, fasciculations or tremors.

Atropine is not dependable in reversing the weakness or paralysis of the respiratory muscles. Severe difficulty in breathing requires artificial respiration in addition to the use of atropine.

Systemic doses of atropine slightly raise systolic and lower diastolic pressures and can produce significant postural hypotension. Such doses also slightly increase cardiac output and decrease central venous pressure. Atropine can dilate cutaneous blood vessels, particularly the “blush” area (atropine flush), may cause atropine “fever” due to suppression of sweat gland activity especially in infants and small children and may inhibit sweating, thereby causing hyperthermia, particularly in a warm environment or with exercise [see Warnings and Precautions (5.2)].

12.3 Pharmacokinetics

Atropine is well absorbed after intramuscular administration. Following 1.67 mg atropine given intramuscularly to adults by the 2 mg ATROPEN delivery system, the peak concentration (Cmax) is 9.6 ± 1.5 (mean ± SEM) ng/mL reached between 3-60 minutes (Tmax). The protein binding of atropine is 14 to 22% in plasma. Atropine is distributed throughout the various body tissues and fluids. Much of the drug is metabolized by enzymatic hydrolysis, particularly in the liver. Atropine has been reported to be excreted in human milk [see Use in Specific Populations (8.2)]. The unchanged drug excreted by urine is approximately 13 to 50%.

Specific Populations

Gender

The AUC(0-inf) and Cmax values for atropine are 15% higher in females than males. The half-life of atropine is approximately 20 minutes shorter in females than males.

Geriatric

The half-life of intravenous atropine is 3.0 ± 0.9 (mean ± SD) hours in adults and 10.0 ± 7.3 (mean ± SD) hours in geriatric patients (65 to 75 years of age).

Pediatric

The half-life of intravenous atropine in pediatric subjects under 2 years is 6.9 ± 3.3 (mean ± SD) hours; in children over 2 years, the half-life is 2.5 ± 1.2 (mean ± SD) hours.

Renal and Hepatic Impairment

The pharmacokinetics of atropine has not been evaluated in subjects with renal or hepatic impairment.

13 NONCLINICAL TOXICOLOGY

13.1 Carcinogenesis, Mutagenesis, Impairment of Fertility

Carcinogenesis

No adequate studies regarding the carcinogenic potential of atropine have been conducted.

Mutagenesis

Studies to assess the mutagenic potential of atropine have not been conducted.

Impairment of Fertility

In studies in which male rats were orally administered atropine (62.5 to 125 mg/kg) for one week prior to mating and throughout a 5-day mating period with untreated females, a dose-related decrease in fertility was observed. A no-effect dose for male reproductive toxicity was not established. The lowest dose tested was 300 times (on a mg/m^2 basis) the dose of atropine in a single application of ATROPEN (2 mg).

Fertility studies of atropine in females have not been conducted.

16 HOW SUPPLIED/STORAGE AND HANDLING

16.1 How Supplied

ATROPEN is a prefilled single-dose autoinjector that contains a clear solution and is supplied in the following package configurations:

Table 3: ATROPEN Package Configurations
NDC Number | Package Configuration | Product Description | Delivered Dose (atropine)
NDC 11704-107-01 | Carton of 1 | ATROPEN 0.25 mg (yellow label) | 0.21 mg/0.3 mL (equivalent to 0.25 mg/0.3 mL of atropine sulfate)
NDC 11704-104-01 | Carton of 1 | ATROPEN 0.5 mg (blue label) | 0.42 mg/0.7 mL (equivalent to 0.5 mg/0.7 mL of atropine sulfate)
NDC 11704-105-01 | Carton of 1 | ATROPEN 1 mg (red label) | 0.84 mg/0.7 mL (equivalent to 1 mg/0.7 mL of atropine sulfate)
NDC 11704-106-01 | Carton of 1 | ATROPEN 2 mg (green label) | 1.67 mg/0.7 mL (equivalent to 2 mg/0.7 mL of atropine sulfate)
NDC 11704-101-01 (For military use only) | 1 Autoinjector | ATROPEN 2 mg | 1.67 mg/0.7 mL (equivalent to 2 mg/0.7 mL of atropine sulfate)

16.2 Storage and Handling

Store between 20ºC to 25ºC (68ºF to 77ºF); excursions permitted between 15ºC and 30ºC (between 59ºF and 86ºF) [See USP Controlled Room Temperature]. Not made with natural rubber latex. Keep from freezing. Protect from light.

After the ATROPEN autoinjector has been activated, the empty container should be disposed of properly. It cannot be refilled, nor can the protruding needle be retracted.

17 PATIENT COUNSELING INFORMATION

Advise the patient to read the FDA-approved patient labeling (Instructions for Use).

Administration Information

Appropriate steps must be taken to ensure that users understand the indications for and use of ATROPEN, including review of symptoms of poisoning and operation of ATROPEN [see Dosage and Administration (2)].

Protection against Organophosphorus Poisoning

Individuals should not rely solely upon atropine to provide complete protection from chemical nerve agents and insecticide poisoning. Primary protection against exposure to chemical nerve agents and insecticide poisoning is the wearing of protective garments including masks designed specifically for this use.

Seek Definitive Medical Care

If feasible and appropriate, advise patients that ATROPEN is an initial emergency treatment, that they need additional care at a healthcare facility.

Avoid Overheating

If feasible and appropriate, advise the patient to avoid a hot environment and excessive physical activity since atropine can inhibit sweating which can lead to overheating and heat injury.

Manufactured by:
Meridian Medical Technologies®, LLC
St. Louis, MO 63146

PATIENT INFORMATION

Instructions for Use

ATROPEN (at-ROW-pen)

(atropine injection)

for intramuscular use

Self and Caregiver Instructions for Use of ATROPEN

Important: Follow these instructions only when ready to use ATROPEN. If possible, a healthcare provider or someone who has been trained to identify and treat the symptoms of nerve agent and insecticide poisoning should give the ATROPEN injection. If a healthcare provider is not available during an emergency, a patient or caregiver might need to give the ATROPEN injection.

Individuals should not rely only on ATROPEN for protection from nerve agent and insecticide poisoning. Exposed persons and caregivers need to wear clothing to protect their skin and goggles and masks to protect their face and eyes when available, to avoid exposure.

Step 1
Choose the Correct Dose

Adults and children
weighing over 90 pounds (41 kg)
(generally over 10 years of age
2 mg ATROPEN (green label)

2 mg

Children
weighing 40 pounds to 90 pounds (18 kg to 41 kg)
(generally 4 to 10 years of age)
1 mg ATROPEN (red label)

1 mg

Children
weighing 15 pounds to 40 pounds (7 kg to 18 kg)
(generally 6 months to 4 years of age)
0.5 mg ATROPEN (blue label)

0.5 mg

Infants
weighing less than 15 pounds (7 kg)
(generally less than 6 months of age)
0.25 mg ATROPEN (yellow label)

0.25 mg

Caution: When the ATROPEN is activated, the needle will quickly extend from the green tip and black tip. Keep your fingers away from the green tip and black tip.

Step 2
Decide if Symptoms are Mild or Severe

If nerve agent or insecticide exposure is known or suspected, you may see the following mild and severe symptoms. You may not have all of the symptoms or see all symptoms in others exposed to a nerve agent or certain insecticide poisoning:

Mild Symptoms

Severe Symptoms

- Blurred vision and sore eyes
- Excessive, unexplained teary eyes
- Excessive, unexplained runny nose
- Increase saliva or sudden drooling
- Chest tightness or breathing problems
- Shaking (tremors) throughout the body or muscle twitching
- Nausea and vomiting
- Unexplained wheezing, coughing or increase in mucus (phlegm) coming from the lungs
- Sudden stomach cramping
- Fast heartbeat (tachycardia) or slow heartbeat (bradycardia)

- Strange or confused behavior
- Severe breathing problems or a large amount of fluid (secretions) coming from the lungs
- Severe muscle twitching and general weakness
- Problems controlling urine or stool (bowel movement)
- Seizures (convulsions)
- Passing out (unconsciousness)

Symptoms in infants and young children:

The mild symptoms excessive, unexplained teary eyes, excessive, unexplained runny nose and increased saliva or sudden drooling, and the severe symptom problems controlling urine or stool (bowel movement) are sometimes seen in healthy infants and young children. In infants and young children, these symptoms are seen less often than the other mild and severe symptoms listed above. Symptoms must be looked at together when nerve agent or insecticide exposure is known or suspected.

The severe symptoms severe muscle twitching and general weakness can happen in infants. Infants may become drowsy or pass out, with muscle floppiness instead of muscle twitching, soon after exposure to nerve agents or insecticides.

Step 3

Treating Mild Symptoms

First Dose: Give 1 dose of ATROPEN (1 injection) if you get 2 or more mild symptoms of nerve agent or insecticide exposure. Give the injection in the outer thigh. Ask a caregiver to check your symptoms to see if they continue or get worse. Get medical help right away.

Additional Doses: If, any time after the first injection of ATROPEN, the exposed person gets any of the severe symptoms listed above, give 2 more doses of ATROPEN (2 injections) in the outer thigh quickly one right after the other. Use a new ATROPEN for each injection. If you have given yourself the first injection, someone else should give you the second and third ATROPEN injections, if possible.

Treating Severe Symptoms

If you get any of the severe symptoms of nerve agent or insecticide exposure listed above or you see an exposed person who has passed out (unconscious), give 3 doses of ATROPEN (3 injections) right away. Give the 3 injections in the outer thigh quickly, one right after the other, using a new ATROPEN for each injection. Get medical help right away.

Warning: Giving more ATROPEN injections by mistake in people who do not have nerve agent or insecticide poisoning may cause an overdose of atropine. This can lead to being unable to see or walk well for several hours. People with heart problems may have serious side effects, that can lead to death.

Step 4
Give the ATROPEN Injection

Instructions for Use of 2 mg, 1 mg, and 0.5 mg ATROPEN
(see below for 0.25 mg dose instructions)

(A) Snap the grooved end of the plastic sleeve down and over the yellow safety release. Remove the ATROPEN from the plastic sleeve.
Caution: Do not place fingers on the green tip.

(B) Firmly grasp the ATROPEN in 1 hand with the green tip pointed down.

(C) Pull off the yellow safety release with your other hand.

(D) Aim and firmly jab the green tip straight down (at a 90 degree angle) against the outer thigh. The ATROPEN will activate and deliver the medicine. You can inject through clothing, but make sure pockets at the injection site are empty.
Note: People who do not have a lot of fat at the injection site and small children should also be injected in the outer thigh. Before giving the ATROPEN injection, pinch a fold of skin on the outer thigh to provide a thicker area for injection.

(E) Hold the ATROPEN firmly in place for at least 10 seconds to allow the injection to finish.

(F) After 10 seconds, remove the ATROPEN and massage the injection site for several seconds.
Note: If you see the needle after removing the ATROPEN, the injection is complete.
If you do not see the needle, check to make sure the yellow safety release has been removed. If the yellow safety release has been removed, repeat Step 4 (D) and Step 4 (E), but press harder to activate the ATROPEN.

(G) After the injection, bend the needle back against the ATROPEN using a hard surface. Use the bent needle as a hook to pin the used ATROPEN to the clothing of the exposed person. You can also show the used ATROPEN to the first medical person you see. This will allow medical personnel to see the number of ATROPENs used and the dose.
Move yourself and the exposed person away from the contaminated area right away. Get medical help right away.

Instructions for Use of 0.25 mg ATROPEN

(A) Remove the plastic cap from the yellow tube and slide the ATROPEN out of the tube.
Caution: Do not place fingers on the black tip.

(B) Firmly grasp the ATROPEN in 1 hand with the black tip pointed down.

(C) Pull off the gray safety release with your other hand.

(D) Pinch a fold of skin on the outer thigh to provide a thicker area for injection. Aim and firmly jab the black tip straight down (at a 90 degree angle) against the outer thigh. The ATROPEN will activate and deliver the medicine. You can inject through clothing, but make sure pockets at the injection site are empty.

(E) Hold the ATROPEN firmly in place for at least 10 seconds to allow the injection to finish.

(F) After 10 seconds, remove the ATROPEN and massage the injection site for several seconds.
Note: If you see the needle after removing the ATROPEN, the injection is complete.
If you do not see the needle, check to make sure the gray safety release has been removed. If the gray safety release has been removed, repeat Step 4 (D) and Step 4 (E), but press harder to activate the ATROPEN.

(G) After the injection, bend the needle back against the ATROPEN using a hard surface. Use the bent needle as a hook to pin the used ATROPEN to the clothing of the exposed person. You can also show the used ATROPEN to the first medical person you see. This will allow medical personnel to see the number of ATROPENs used and the dose.
Move yourself and the exposed person away from the contaminated area right away. Get medical help right away.

This Instructions for Use has been approved by the U.S. Food and Drug Administration.

ATROPEN® is a registered trademark of
Meridian Medical Technologies®, LLC

St. Louis, MO 63146
1-833-739-0945
Revised: 09/2022

Principal Display Panel - 0.25 mg Carton Label

NDC 11704-107-01

MERIDIAN
MEDICAL TECHNOLOGIES™

ATROPEN®
(atropine injection) 0.25 mg

Single-Dose Auto-Injector
for Intramuscular Use Only

Rx Only

For use in Nerve Agent and Insecticide Poisoning

Each auto-injector delivers an injection of 0.21 mg/0.3 mL atropine (equivalent
to 0.25 mg atropine sulfate), 1.5 mg citric acid monohydrate, 2.0 mg sodium
citrate dihydrate and 2.0 mg sodium chloride.

Principal Display Panel - 0.5 mg Carton Label

NDC 11704-104-01

MERIDIAN
MEDICAL TECHNOLOGIES™

ATROPEN®
(atropine injection) 0.5 mg

Single-Dose Auto-Injector
for Intramuscular Use

Rx Only

for use in Nerve Agent and Insecticide Poisoning

Each auto-injector delivers an injection of 0.42 mg/0.7mL atropine
(equivalent to 0.5 mg atropine sulfate), 12.5 mg glycerin, 2.4 mg citric acid
monohydrate, 2.4 mg sodium citrate dihydrate and 2.8 mg phenol.

Principal Display Panel - 1 mg Carton Label

NDC 11704-105-01

MERIDIAN
MEDICAL TECHNOLOGIES™

ATROPEN®
(atropine injection) 1 mg

Single-Dose Auto-Injector
for Intramuscular Use

Rx Only

for use in Nerve Agent and Insecticide Poisoning

Each auto-injector delivers an injection of 0.84 mg/0.7mL atropine
(equivalent to 1 mg atropine sulfate), 12.5 mg glycerin, 2.7 mg citric acid monohydrate,
2.7 mg sodium citrate dihydrate and 2.8 mg phenol.

Principal Display Panel - 2 mg Carton Label

NDC 11704-106-01

MERIDIAN
MEDICAL TECHNOLOGIES™

ATROPEN®
(atropine injection) 2 mg

Single-Dose Auto-Injector
for Intramuscular Use

Rx Only

for use in Nerve Agent and Insecticide Poisoning

Each auto-injector delivers an injection of 1.67 mg/0.7mL atropine
(equivalent to 2 mg atropine sulfate), 12.5 mg glycerin, 3.3 mg citric acid monohydrate,
3.0 mg sodium citrate dihydrate and 2.8 mg phenol.

Principal Display Panel - 2 mg Auto-Injector Label

NDC 11704-101-01

MERIDIAN
MEDICAL TECHNOLOGIES™

St. Louis, MO 63146

1-833-739-0945

Store at 20°C-25°C (68°F-77°F); excursions permitted to 15°C-30°C (59°F-86°F).

[See USP Controlled Room Temperature]. Keep from freezing.

NSN 6505-00-926-9083

ATROPEN®
(atropine injection) 2 mg

Single-Dose Auto-Injector
for Intramuscular Use in
Nerve Agent and Insecticide Poisoning

Each auto-injector delivers an injection of 1.67 mg/0.7 mL atropine (equivalent to 2 mg atropine sulfate).

1 Remove Yellow Safety

2 Place Green End on outer thigh
and push hard till injector functions

Rx Only

0002208

NDC 11704-101-01